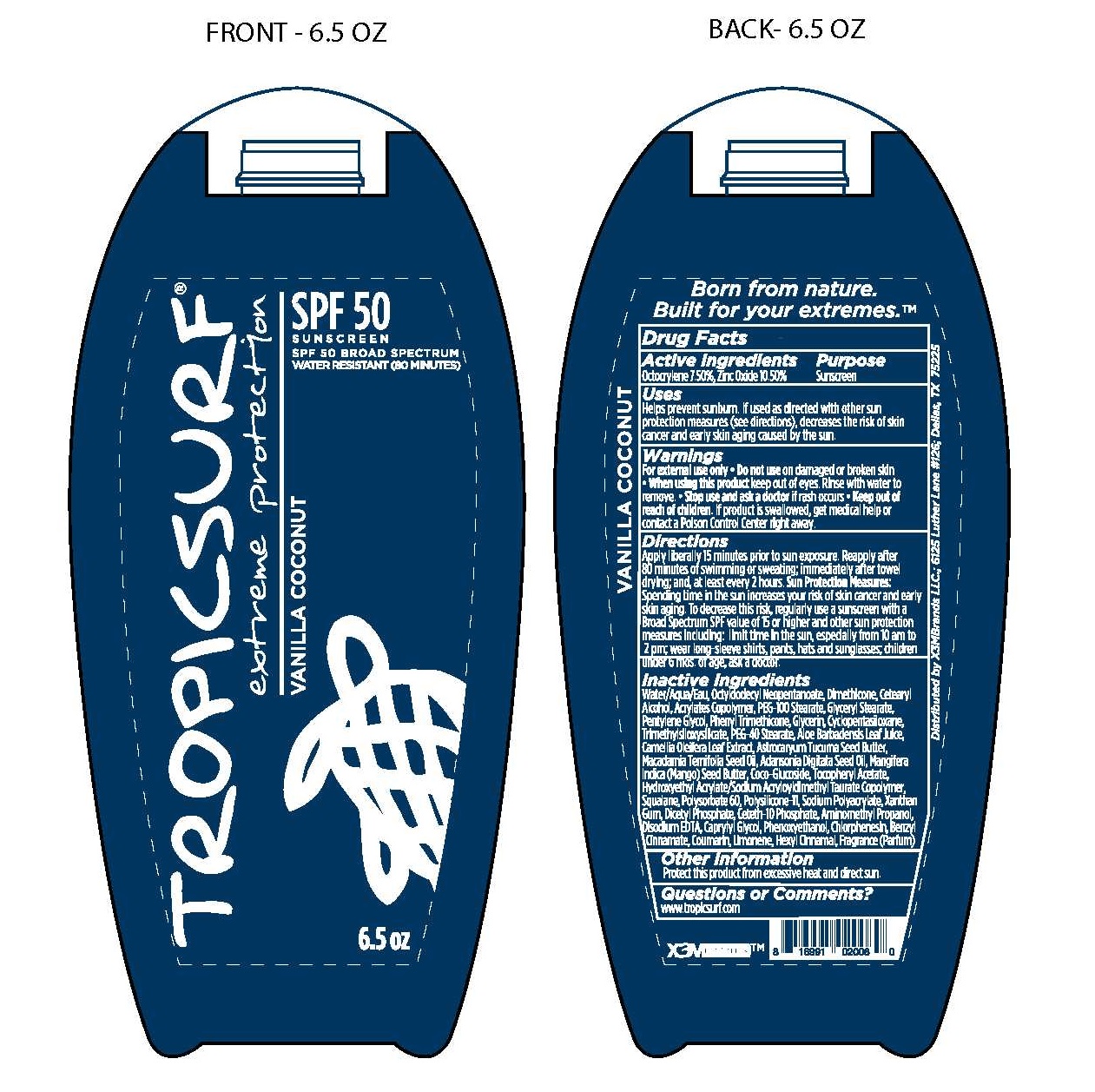 DRUG LABEL: TROPICSURF EXTREME PROTECTION SPF50
NDC: 70884-102 | Form: LOTION
Manufacturer: PALMER SURF LLC (DBA X3EMBRANDS)
Category: otc | Type: HUMAN OTC DRUG LABEL
Date: 20171218

ACTIVE INGREDIENTS: OCTOCRYLENE 7.5 g/100 mL; ZINC OXIDE 10.5 g/100 mL
INACTIVE INGREDIENTS: WATER; OCTYLDODECYL NEOPENTANOATE; DIMETHICONE; CETOSTEARYL ALCOHOL; CARBOMER COPOLYMER TYPE A (ALLYL PENTAERYTHRITOL CROSSLINKED); PEG-100 STEARATE; GLYCERYL STEARATE SE; PENTYLENE GLYCOL; PHENYL TRIMETHICONE; GLYCERIN; CYCLOMETHICONE 5; TRIMETHYLSILOXYSILICATE (M/Q 0.6-0.8); PEG-40 STEARATE; ALOE VERA LEAF; CAMELLIA OLEIFERA LEAF; ASTROCARYUM ACULEATUM SEED OIL; MACADAMIA OIL; ADANSONIA DIGITATA SEED OIL; MANGIFERA INDICA SEED BUTTER; COCO GLUCOSIDE; ALPHA-TOCOPHEROL ACETATE; HYDROXYETHYL ACRYLATE/SODIUM ACRYLOYLDIMETHYL TAURATE COPOLYMER (100000 MPA.S AT 1.5%); SQUALANE; POLYSORBATE 60; DIMETHICONE/VINYL DIMETHICONE CROSSPOLYMER (SOFT PARTICLE); SODIUM POLYACRYLATE (2500000 MW); XANTHAN GUM; DIHEXADECYL PHOSPHATE; CETETH-10 PHOSPHATE; AMINOMETHYLPROPANOL; DISODIUM EDTA-COPPER; CAPRYLYL GLYCOL; PHENOXYETHANOL; CHLORPHENESIN; BENZYL CINNAMATE; COUMARIN; LIMONENE, (+)-; .ALPHA.-HEXYLCINNAMALDEHYDE

ACTIVE INGREDIENT

- OCTOCRYLENE 7.5%
- ZINC OXIDE 10.5%

DIRECTIONS

- APPLY LIBERALLY 15 MINUTES PRIOR TO SUN EXPOSURE. REAPPLY AFTER
- 80 MINUTES OF SWIMMING OR SWEATING; IMMEDIATELY AFTER TOWEL
- DRYING; AND, AT LEAST EVERY 2 HOURS.

SUN PROTECTION MEASURES:

- SPENDING TIME IN THE SUN INCREASES YOUR RISKI OF SKIN CANCER AND EARLY SKIN
- AGING. TO DECREASE THIS RISK, REGULARLY USE A SUNSCREEN WITH A BROAD
- SPECTRUM SPF VALUE OF 15 OR HIGHER AND OTHER SUN PROTECTION MEASURES
- INCLUDING: LIMIT TIME IN THE SUN, ESPECIALLY FROM 10 AM TO 2 PM; WEAR
- LONG-SLEEVE SHIRTS, PANTS, HATS AND SUNGLASSES; CHILDREN UNDER 6 MOS.
- OF AGE, ASK A DOCTOR

PURPOSE:

- SUNSCREEN

Uses:

- HELPS PREVENT SUNBURN
- IF USED AS DIRECTED WITH OTHER SUN PROTECTION MEASURES (SEE DIRECTIONS),
- DECREASES THE RISK OF SKIN CANCER AND EARLY SKIN AGING CAUSED BY THE SUN.

WARNINGS

FOR EXTERNAL USE ONLY

DO NOT USE ON DAMAGED OR BROKEN SKIN

WHEN USING THIS PRODUCT

- KEEP OUT OF THE EYES.
- RINSE WITH WATER TO REMOVE

STOP USE AND ASK A DOCTOR IF

- IF RASH OCCURS

KEEP OUT OF REACH OF CHILDREN.

- IF PRODUCT IS SWALLOWED, GET MEDICAL HELP OR CONTACT A POISON CONTROL CENTER RIGHT AWAY.

INACTIVE INGREDIENTS:

WATER/AQUA/EAU, OCTYLDODECYL NEOPENTANOATE, DIMETHICONE, CETEARYL ALCOHOL, ACRYLATES COPOLYMER,

PEG-100 STEARATE, GLYCERYL STEARATE, PENTYLENE GLYCOL, PHENYL TRIMETHICONE, GLYCERIN, CYCLOPENTASILOXANE,

TRIMETHYLSILOXYSILICATE, PEG-40 STEARATE, ALOE BARBADENSIS LEAF JUICE, CAMELLIA OLEIFERA LEAF JUICE,

ASTROCARYUM TUCUMA SEED BUTTER, MACADAMIA TERNIFOLIA SEED OIL, ADANSONIA DIGITATA SEED OIL, MANGIFERA

INDICA (MANGO) SEED BUTTER, COCO GLUCOSIDE, TOCOPHERYL ACETATE, HYDROXYETHYL ACRYLATE/SODIUM ACRYLOYLDIMETHYL

TAURATE COPOLYMER, SQUALANE, POLYSORBATE 60, POLYSILICONE-11, SODIUM POLYACRYLATE, XANTHAN GUM,

DICETYL PHOSPHATE, CETTH-10 PHOSPHATE, AMINOMETHYLPROPANOL, DISODIUM EDTA, CAPRYLYL GLYCOL, PHENOXYETHANOL,

CHLOPHENESIN, BENXYL CINNAMATE, COUMARIN, LIMONENE, HEXYL CINNAMAL, FRAGRANCE (PARFUM)